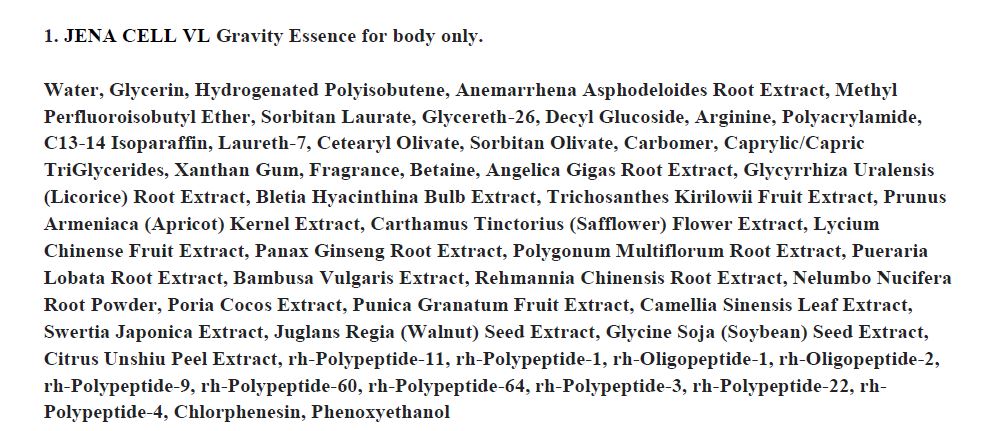 DRUG LABEL: JENA CELL VL Gravity Essence for body only.
NDC: 72311-0001 | Form: LIQUID
Manufacturer: Jena International Ltd
Category: otc | Type: HUMAN OTC DRUG LABEL
Date: 20180520

ACTIVE INGREDIENTS: GLYCERIN 0.3 g/100 mL
INACTIVE INGREDIENTS: WATER; ARGININE

Drug Facts

ACTIVE INGREDIENT

glycerin

INACTIVE INGREDIENT

water, hydrogenated polyisobutene, arginine, etc

PURPOSE

skin protectant

keep out of reach of the children

INDICATIONS AND USAGE

apply proper amount to the skin

WARNINGS

■store between 20-25 °C (68-77 °F)
■avoid freezing and excessive heat above 40 °C (104 °F)

DOSAGE AND ADMINISTRATION

keep out of eyes, ears and mouth, If contact occurs, rinse with plenty of worm or cold water right away and in a serious situation, contact a physician. If swallowing, drink plenty of water and contact a physician